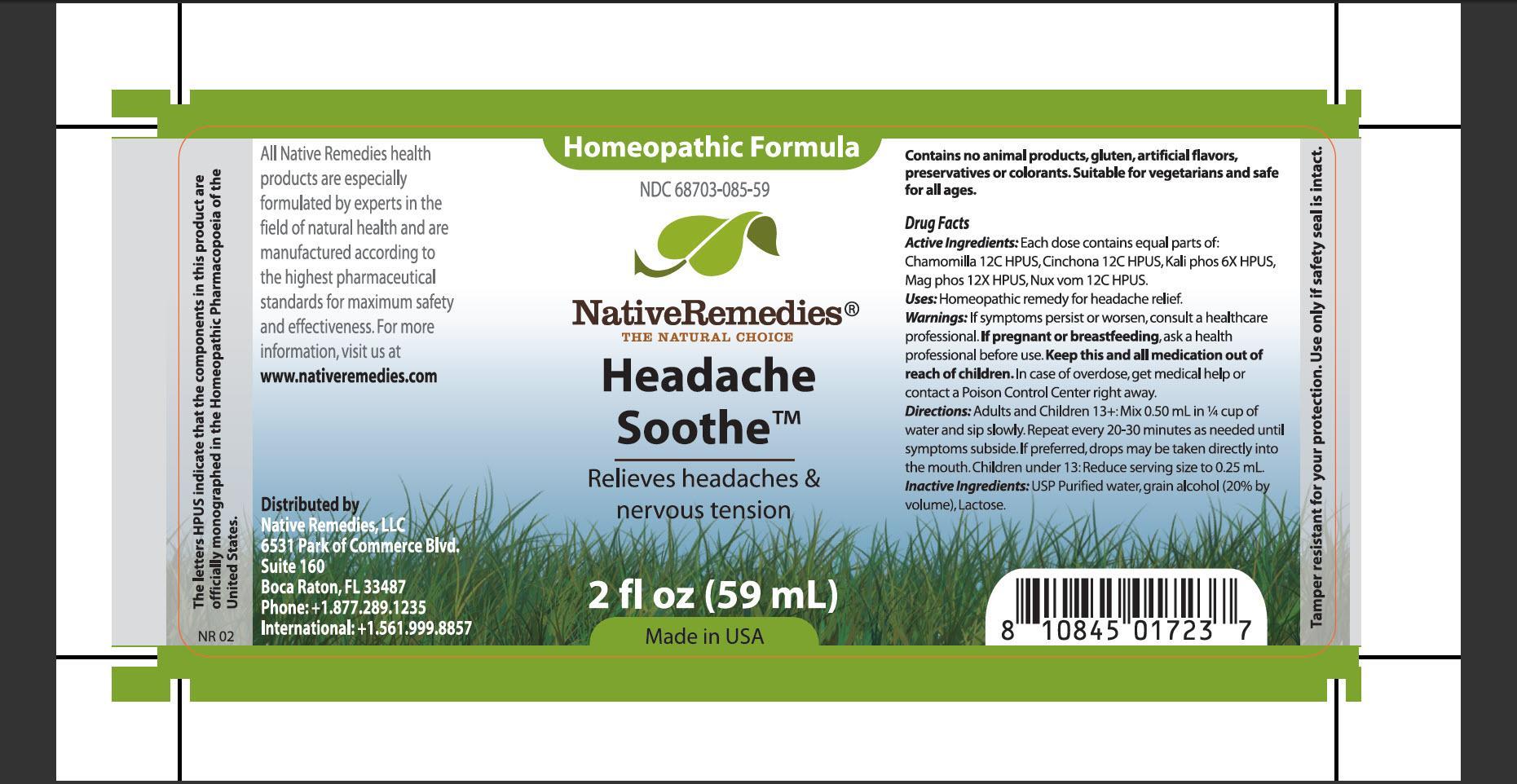 DRUG LABEL: Headache Soothe
NDC: 68703-085 | Form: TINCTURE
Manufacturer: Native Remedies, LLC
Category: homeopathic | Type: HUMAN OTC DRUG LABEL
Date: 20130411

ACTIVE INGREDIENTS: MATRICARIA RECUTITA 12 [hp_C]/1 mL; CINCHONA OFFICINALIS BARK 12 [hp_C]/1 mL; POTASSIUM PHOSPHATE, DIBASIC 6 [hp_X]/1 mL; MAGNESIUM PHOSPHATE, DIBASIC TRIHYDRATE 12 [hp_X]/1 mL; STRYCHNOS NUX-VOMICA SEED 12 [hp_C]/1 mL
INACTIVE INGREDIENTS: WATER; ALCOHOL; LACTOSE

Headache Soothe

PURPOSE

Relieves headache and nervous tension

ACTIVE INGREDIENT

Active Ingredients: Each dose contains equal parts of: Chamomilla 12C HPUS, Cinchona 12C HPUS, Kali phos 6X HPUS, Mag phos 12X HPUS, Nux vom 12C HPUS

INDICATIONS AND USAGE

Uses: Homeopathic remedy for headache relief

WARNINGS

Warnings: If symptoms persist or worsen, consult a health care professional

PREGNANCY OR BREAST FEEDING

If pregnant or breastfeeding, ask a health professional before use it

KEEP OUT OF REACH OF CHILDREN

Keep this and all medication out of reach of children

OVERDOSAGE

In case of overdose, get medical help or contact Poison Control Center right away

DOSAGE AND ADMINISTRATION

Directions: Adults and Children 13+: Mix 0.50 mL in 1/4 cup of water and sip slowly. Repeat every 20-30 minutes as needed until symptoms subside. If preferred, drops may betaken directly into the mouth. Children under 13: Reduce serving size to 0.25 mL

INACTIVE INGREDIENT

Inactive Ingredients: USP Purified water, grain alcohol (20% by volume), Lactose

PATIENT COUNSELING INFORMATION

The letters HPUS indicate that the components in this product are officially monographed in the Homeopathic Pharmacopoeia of the United States

All Native Remedies health products are especially formulated by expert in the field of natural health and are manufactured according to the highest pharmaceutical standards for maximum safety and effectiveness. For more information, visit us at www.nativeremedies.com

Distributed by
Native Remedies, LLC
6531 Park of Commerce Blvd.
Suite 160
Boca Raton, FL 33487
Phone: +1.877.289.1235
International: +1.561.999.8857

Contains no animal products, glutenm artificial flavors, preservatives or colorants. Suitable for vegetarians and safe for all ages

STORAGE AND HANDLING

Tamper resistant for your protection. Use only if seal is intact